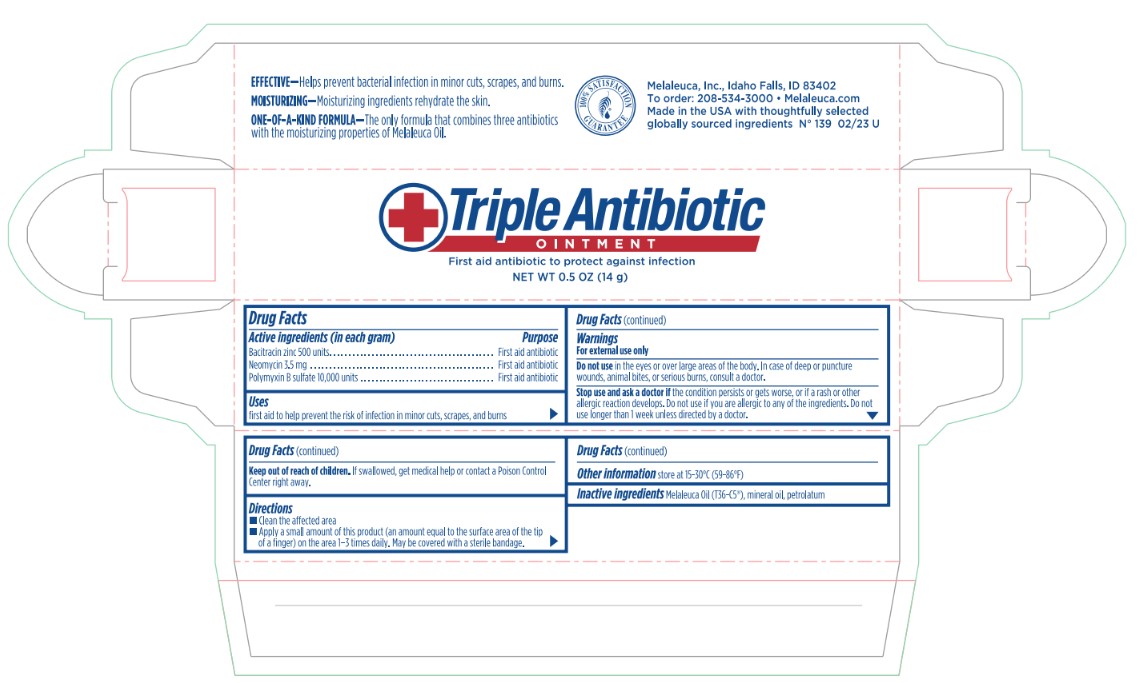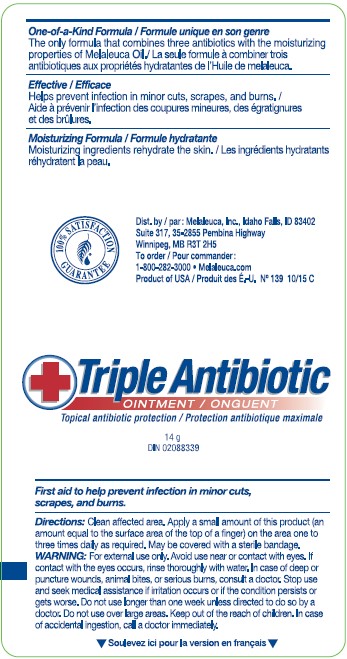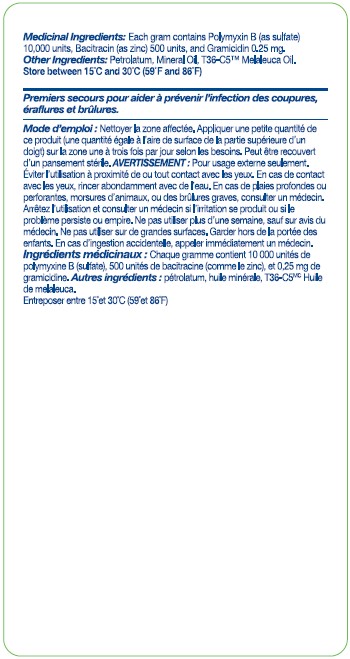 DRUG LABEL: Triple Antibiotic
NDC: 54473-291 | Form: OINTMENT
Manufacturer: Melaleuca, Inc.
Category: otc | Type: HUMAN OTC DRUG LABEL
Date: 20251231

ACTIVE INGREDIENTS: BACITRACIN ZINC 500 U/1 g; NEOMYCIN SULFATE 3.5 mg/1 g; POLYMYXIN B SULFATE 10000 U/1 g
INACTIVE INGREDIENTS: TEA TREE OIL; MINERAL OIL; PETROLATUM

Triple Antibiotic Ointment

Active Ingredients (each gram contains:)
Bacitracin zinc500 units
Neomycin3.5 mg
Polymyxin B sulfate10,000 units

Purpose
antibiotic

Uses
First aid to help prevent the risk of infection in minor

- cuts
- scrapes
- burns

Warnings
For external use only.

Do not use in the eyes or over large areas of the body. In case of deep or puncture wounds, animal bites, or serious burns, consult a doctor

Stop use and ask a doctor if the condition persists or gets worse. Do not use longer than 1 week unless directed by a doctor.

Keep out of reach of children.
If swallowed, get medical help or contact a Poison Control Center right away.

Directions

- Clean the affected area
- apply a small amount of this product (an amount equal to the surface area of the tip of a finger) on the area 1-3 times daily
- may be covered with a sterile bandage

INACTIVE INGREDIENT

Inactive ingredients: Melaleuca Oil (T36-C5(R)), mineral oil, petrolatum

DESCRIPTION

One-of-a-Kind Formula

The only formula that combines three antibiotics with the moisturizing properties of Melaleuca Oil.

Effective

Helps prevent bacterial infection in minor cuts, scrapes, and burns.

Moisturizing

Moisturizing ingredients rehydrate the skin.